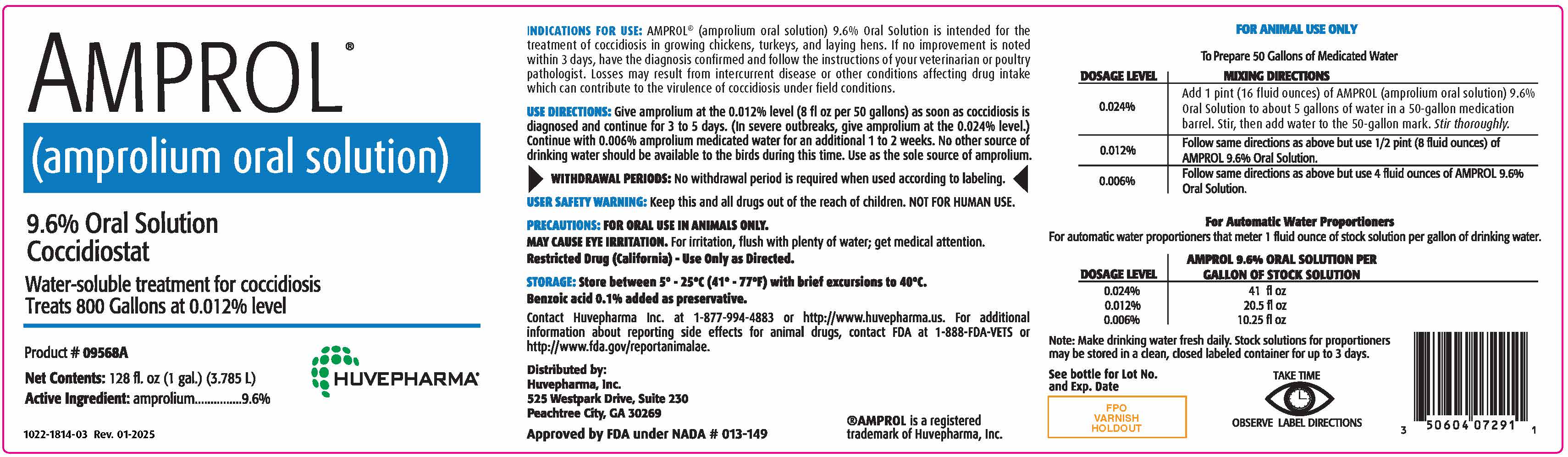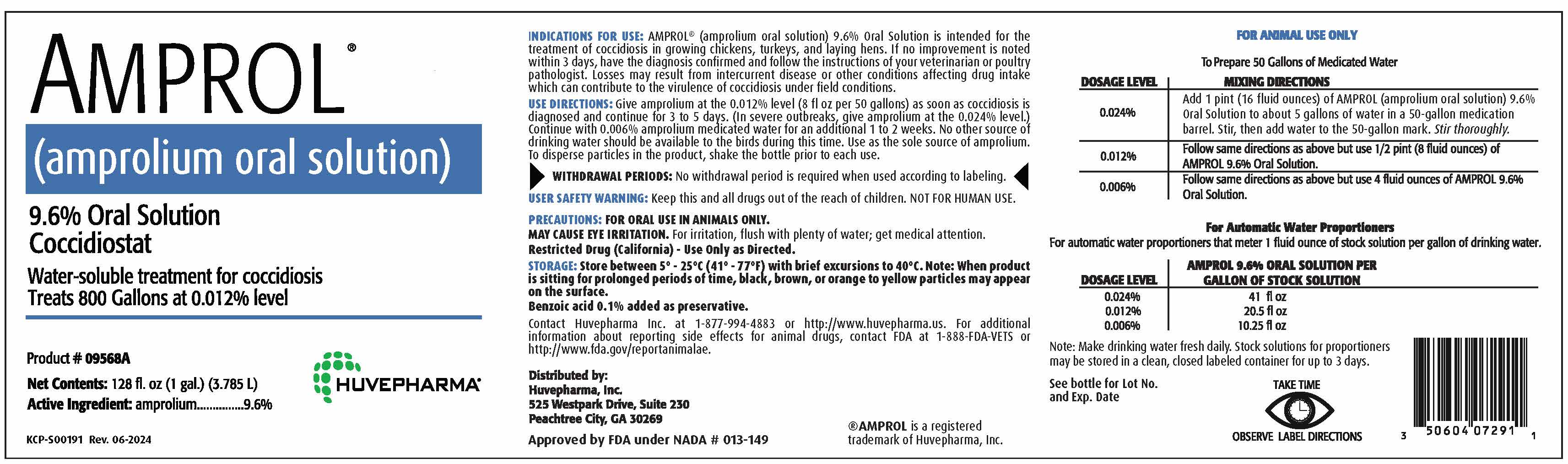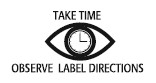 DRUG LABEL: Amprol
NDC: 23243-6681 | Form: SOLUTION
Manufacturer: Huvepharma, Inc
Category: animal | Type: OTC ANIMAL DRUG LABEL
Date: 20250212

ACTIVE INGREDIENTS: AMPROLIUM 96 mg/1 mL

AMPROL®

(amprolium oral solution)

9.6% Oral Solution

Coccidiostat

Water-soluble treatment for coccidiosis

Treats 800 Gallons at 0.012% level

Product # 09568A

Net Contents: 128 fl.oz (1 gal.) (3.785 L)

Active Ingredient: amprolium............9.6%

KCP-S00191 Rev. 06-2024

VETERINARY INDICATIONS

INDICATIONS FOR USE: AMPROL® (amprolium oral solution) 9.6% Oral Solution is intended for the
treatment of coccidiosis in growing chickens, turkeys, and laying hens. If no improvement is noted
within 3 days, have the diagnosis confirmed and follow the instructions of your veterinarian or poultry
pathologist. Losses may result from intercurrent disease or other conditions affecting drug intake
which can contribute to the virulence of coccidiosis under field conditions.

INSTRUCTIONS FOR USE

USE DIRECTIONS: Give amprolium at the 0.012% level (8 fl oz per 50 gallons) as soon as coccidiosis is
diagnosed and continue for 3 to 5 days. (In severe outbreaks, give amprolium at the 0.024% level.)
Continue with 0.006% amprolium medicated water for an additional 1 to 2 weeks. No other source of
drinking water should be available to the birds during this time. Use as the sole source of amprolium.
To disperse particles in the product, shake the bottle prior to each use.

RESIDUE WARNING

WITHDRAWAL PERIODS: No withdrawal period is required when used according to labeling.

USER SAFETY WARNINGS

USER SAFETY WARNING: Keep this and all drugs out of the reach of children. NOT FOR HUMAN USE.

PRECAUTIONS: FOR ORAL USE IN ANIMALS ONLY.
MAY CAUSE EYE IRRITATION. For irritation, flush with plenty of water; get medical attention.
Restricted Drug (California) - Use Only as Directed.

STORAGE AND HANDLING

STORAGE: Store between 5º - 25ºC (41º - 77ºF) with brief excursions to 40ºC. Note: When product
is sitting for prolonged periods of time, black, brown, or orange to yellow particles may appear
on the surface.
Benzoic acid 0.1% added as preservative.

ADVERSE REACTIONS

Contact Huvepharma Inc. at 1-877-994-4883 or http://www.huvepharma.us. For additional
information about reporting side effects for animal drugs, contact FDA at 1-888-FDA-VETS or
http://www.fda.gov/reportanimalae.

Distributed by:
Huvepharma, Inc.
525 Westpark Drive, Suite 230
Peachtree City, GA 30269 ®AMPROL is a registered
trademark of Huvepharma, Inc.
Approved by FDA under NADA # 013-149

DOSAGE FORMS AND STRENGTHS

FOR ANIMAL USE ONLY

To prepare 50 Gallons of Medicated Water

DOSAGE LEVEL | MIXING DIRECTIONS
0.024% | Add 1 pint (16 fluid ounces) of AMPROL (amprolium oral solution) 9.6% Oral Solution to about 5 gallons of water in a 50-gallon medication barrel. Stir, then add water to the 50-gallon mark. Stir thoroughly.
0.012% | Follow same directions as above but use 1/2 pint (8 fluid ounces) of AMPROL 9.6% Oral Solution
0.006% | Follow same directions as above but use 4 fluid ounces of AMPROL 9.6% Oral Solution

For Automatic Water Proportioners
For automatic water proportioners that meter 1 fluid ounce
of stock solution per gallon of drinking water.

DOSAGE LEVEL | AMPROL 9.6% ORAL SOLUTION PER GALLON OF STOCK SOLUTION
0.024% 0.012% 0.006% | 41 fl oz 20.5 fl oz 10.25 fl oz

Note: Make drinking water fresh daily. Stock solutions for proportioners may be stored
in a clean, closed labeled container for up to 3 days.

See bottle for Lot No.
and Exp. Date